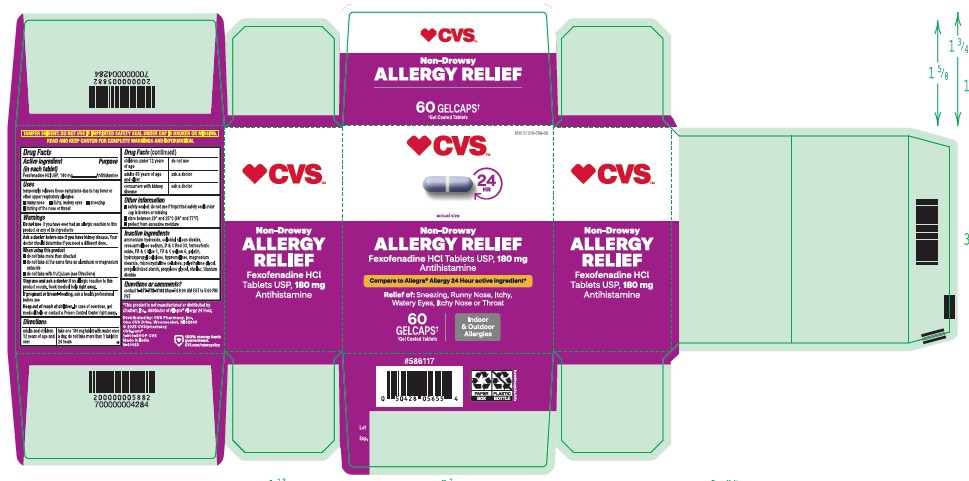 DRUG LABEL: Fexofenadine HCL
NDC: 51316-768 | Form: TABLET
Manufacturer: CVS
Category: otc | Type: HUMAN OTC DRUG LABEL
Date: 20251219

ACTIVE INGREDIENTS: FEXOFENADINE HYDROCHLORIDE 180 mg/1 1
INACTIVE INGREDIENTS: SHELLAC; D&C RED NO. 33; AMMONIA; FD&C BLUE NO. 1; FERROSOFERRIC OXIDE; TITANIUM DIOXIDE; POLYETHYLENE GLYCOL 8000; CROSCARMELLOSE SODIUM; FD&C YELLOW NO. 6; MAGNESIUM STEARATE; SILICON DIOXIDE; GELATIN; HYPROMELLOSE 2910 (3 MPA.S); MICROCRYSTALLINE CELLULOSE; HYDROXYPROPYL CELLULOSE (90000 WAMW); STARCH, CORN; PROPYLENE GLYCOL

Fexofenadine HCL Tablets USP, 180mg
Antihistamine
Indoor/Outdoor Allergy Relief
• Sneezing
• Runny nose
• Itchy, watery eyes
• Itchy nose or throat
Non-Drowsy

Active ingredient (in each tablet)

Fexofenadine HCl USP, 180 mg

Purpose

.Antihistamine

Uses

temporarily relieves these symptoms due to hay fever or other upper respiratory allergies:
■ runny nose ■ itchy, watery eyes ■ sneezing
■ itching of the nose or throat

Do not use

if you have ever had an allergic reaction to this product or any of its ingredients

Ask a doctor before use if you have

kidney disease. Your doctor should determine if you need a different dose.

When using this product

■ do not take more than directed
■ do not take at the same time as aluminum or magnesium antacids
■ do not take with fruit juices (see Directions)

Stop use and ask a doctor if

an allergic reaction to this product occurs. Seek medical help right away.

If pregnant or breast-feeding

ask a health professional before use

Keep out of reach of children.

In case of overdose, get medical help or contact a Poison Control Center right away.

Directions

adults and children 12 years of age and take one 180 mg tablet with water once a day; do not take more than 1 tablet in 24 hours

Other information

■ safety sealed: do not use if imprinted safety seal under cap is broken or missing
■ store between 20° and 25°C (68° and 77°F)
■ protect from excessive moisture

Inactive ingredients

ammonium hydroxide, colloidal silicon dioxide, croscarmellose sodium, D & C Red 33, ferrosoferric oxide, FD & C blue 1, FD & C yellow 6, gelatin, hydroxypropyl cellulose, hypromellose, magnesium stearate, microcrystalline cellulose, polyethylene glycol,
pregelatinized starch, propylene glycol, shellac, titanium dioxide.

Questions or comments?

contact 1-877-770-3183 Mon-Fri 8:00 AM EST to 5:00 PM PST